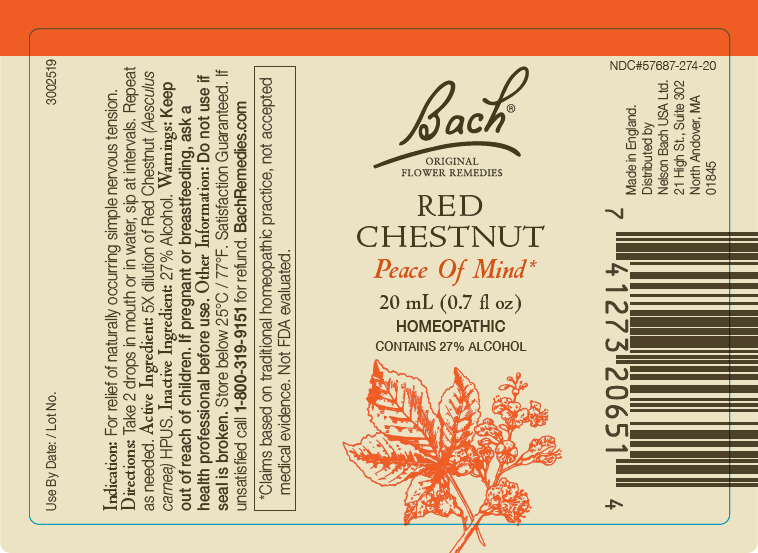 DRUG LABEL: Bach Original Flower Remedies
NDC: 57687-274 | Form: SOLUTION
Manufacturer: Nelson Bach USA Limited
Category: homeopathic | Type: HUMAN OTC DRUG LABEL
Date: 20220216

ACTIVE INGREDIENTS: AESCULUS X CARNEA WHOLE 5 [hp_X]/0.095 mL
INACTIVE INGREDIENTS: ALCOHOL

Bach® Original Flower Remedies

Indications

PURPOSE

For relief of naturally occurring simple nervous tension.

Directions

Take 2 drops in mouth or in water, sip at intervals. Repeat as needed.

Warnings

Keep out of reach of children.

PREGNANCY OR BREAST FEEDING

If pregnant or breast-feeding, ask a health professional before use.

Active Ingredients

5 x dilution of Aesculus carnea HPUS.

Inactive Ingredients

27% Alcohol.

QUESTIONS

Satisfaction guaranteed, call 1-800-319-9151 if unsatisfied for complete refund.

Distributed by
Nelson Bach USA, Ltd.,
Andover, MA 01845

PRINCIPAL DISPLAY PANEL - 20 mL Bottle Label

Bach®
ORIGINAL
FLOWER REMEDIES

RED
CHESTNUT

Peace Of Mind*

20 mL (0.7 fl oz)
HOMEOPATHIC
CONTAINS 27% ALCOHOL